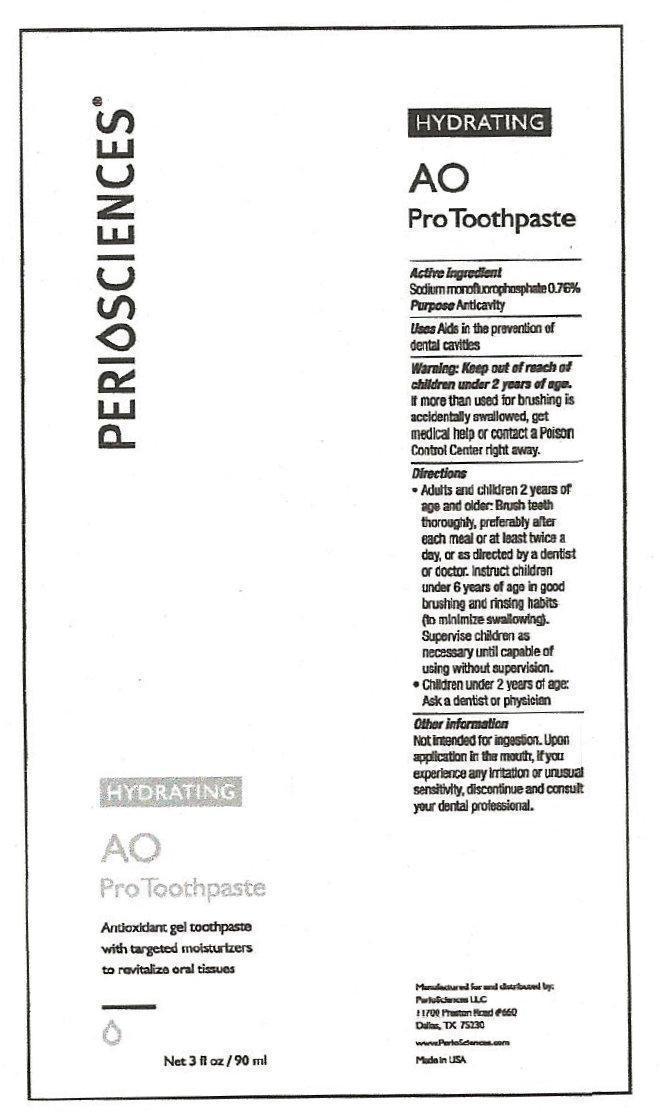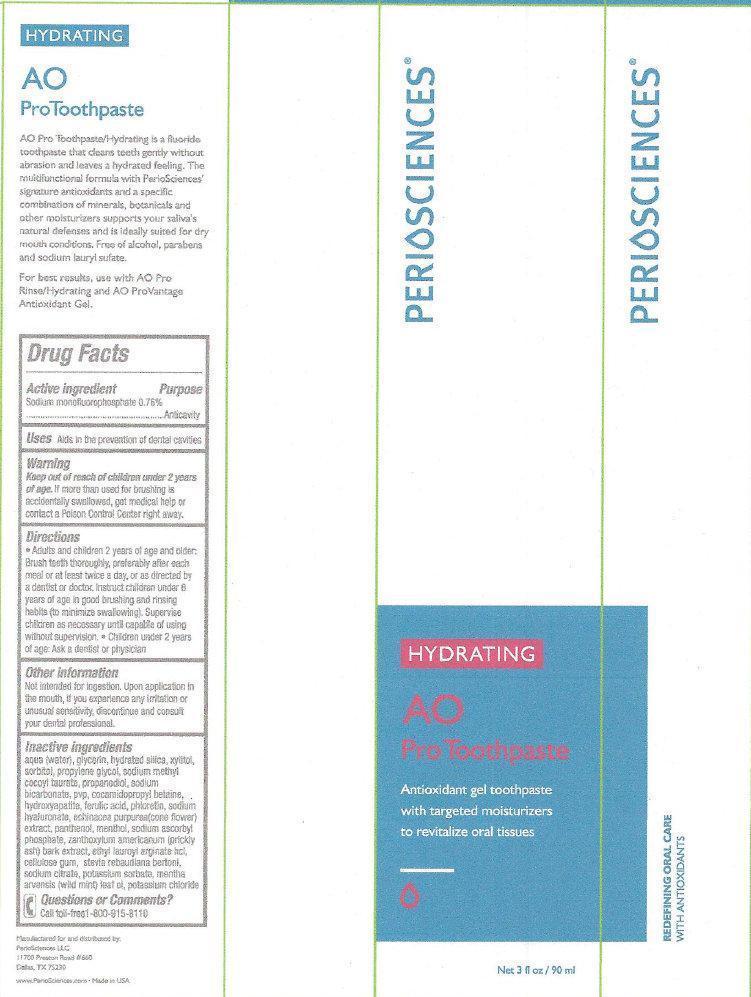 DRUG LABEL: PERIOSCIENCES HYDRATING AO Pro
NDC: 53238-003 | Form: PASTE, DENTIFRICE
Manufacturer: PERIOSCIENCES LLC
Category: otc | Type: HUMAN OTC DRUG LABEL
Date: 20260209

ACTIVE INGREDIENTS: SODIUM MONOFLUOROPHOSPHATE 1.3 mg/1 mL
INACTIVE INGREDIENTS: WATER; GLYCERIN; HYDRATED SILICA; XYLITOL; SORBITOL; PROPYLENE GLYCOL; SODIUM METHYL COCOYL TAURATE; PROPANEDIOL; SODIUM BICARBONATE; COCAMIDOPROPYL BETAINE; TRIBASIC CALCIUM PHOSPHATE; FERULIC ACID; PHLORETIN; HYALURONATE SODIUM; PANTHENOL; MENTHOL; SODIUM ASCORBYL PHOSPHATE; ETHYL LAUROYL ARGINATE HYDROCHLORIDE; CARBOXYMETHYLCELLULOSE SODIUM; SODIUM CITRATE; POTASSIUM SORBATE; POTASSIUM CHLORIDE

PERIOSCIENCES HYDRATING AO ProToothpaste

Active ingredient

Sodium monofluorophosphate 0.76%

Purpose

Anticavity

Uses

Aids in prevention of dental cavities

Warning

Keep out of reach of children under 2 years of age.

If more than used for brushing is accidentally swallowed, get medical help or contact a Poison Control Center right away.

Directions

- Adults and children 2 years of age and older: Brush teeth thoroughly, preferably after each meal or at least twice a day, or as directed by a dentist or doctor. Instruct children under 6 years of age in good brushing and rinsing habits (to minimize swallowing). Supervise children as necessary until capable of using without supervision.
- Children under 2 years of age: Ask a dentist or physician

Other information

Not intended for ingestion. Upon application in the mouth, if you experience any irritation or unusual sensitivity, discontinue and consult your dental professional.

Inactive ingredients

aqua (water), glycerin, hydrated silica, xylitol, sorbitol, propylene glycol, sodium methyl cocoyl taurate, propanediol, sodium bicarbonate, pvp, cocamidopropyl betaine, hydroxyapatite, ferulic acid, phloretin, sodium hyaluronate, echinacea purpurea (cone flower) extract, panthenol, menthol, sodium ascorbyl phosphate, zanthoxylum americanum (prickly ash) bark extract, ethyl lauroyl arginate hcl, cellulose gum, stevia rebaudiana bertoni, sodium citrate, potassium sorbate, mentha arvensis (wild mint) leaf oil, potassium chloride

Questions or Comments?

Call toll-free 1-800-915-8110

HYDRATING AO ProToothpaste

AO Pro Toothpaste/Hydrating is a fluoride toothpaste that cleans teeth gently without abrasion and leaves a hydrated feeling. The multifunctional formula with PerioSciences signature antioxidants and a specific combination of minerals, botanicals and other moisturizers supports your saliva's natural defenses and is ideally suited for dry mouth conditions. Free of alcohol, parabens and sodium lauryl sufate.
For best results, use with AO ProRinse/Hydrating and AO ProVantage Antioxidant Gel.
Manufactured and distributed by:
Periosciences LLC
11700 Preston Road #660
Dallas, TX 75230
www. PerioSciences.com - Made in USA

PACKAGE LABEL

PERIOSCIENCES HYDRATING AO ProToothpaste Antioxidant gel toothpaste with targeted moisturizers to revitalize oral tissues Net 3 fl oz / 90 ml REDEFINING ORAL CARE WITH ANTIOXIDANTS